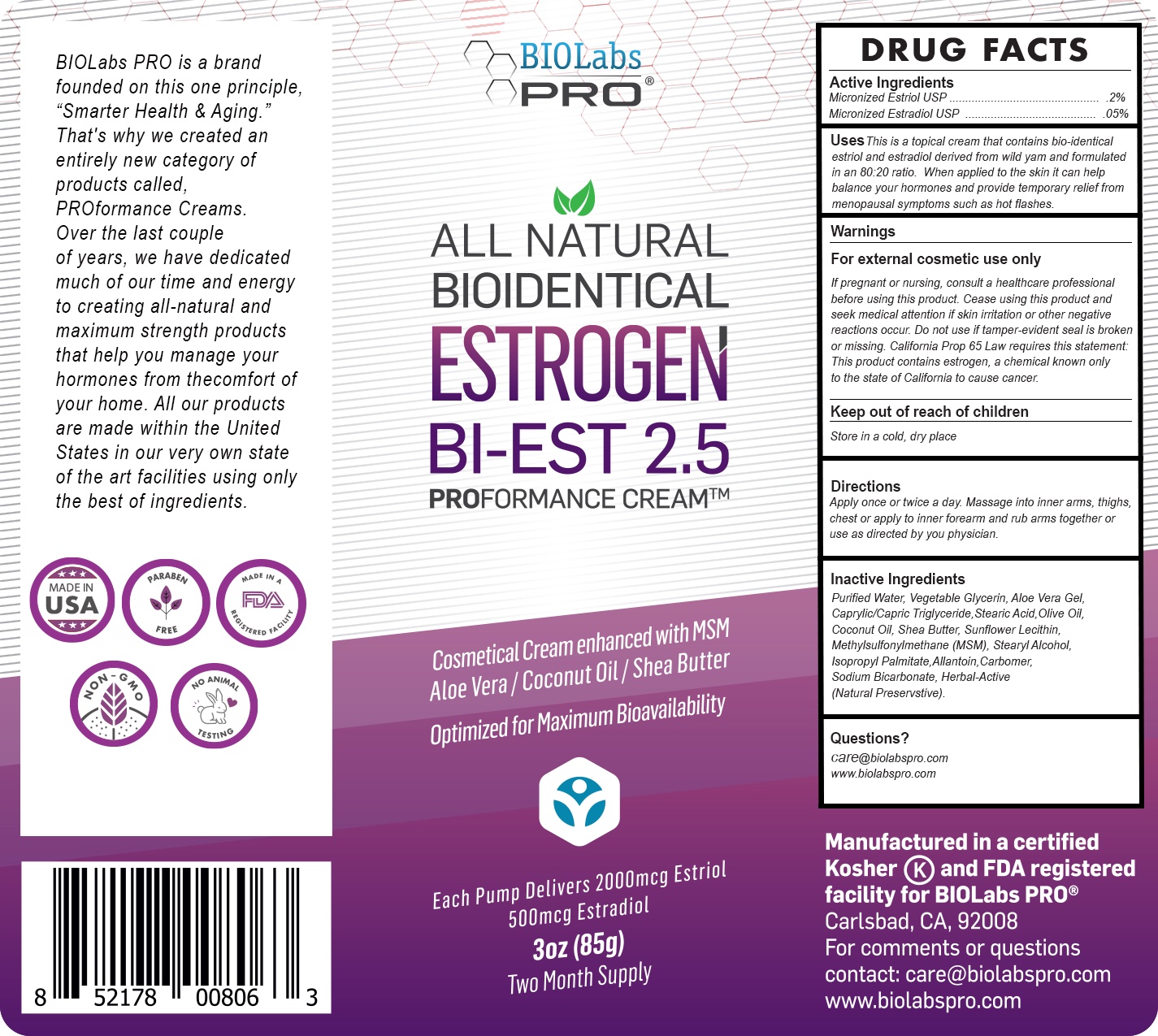 DRUG LABEL: BiEST 2.5 Estrogen Cream
NDC: 82018-0007 | Form: CREAM
Manufacturer: SHYNE BRANDS
Category: otc | Type: HUMAN OTC DRUG LABEL
Date: 20210621

ACTIVE INGREDIENTS: ESTRIOL 2 mg/85 g; ESTRADIOL 0.5 mg/85 g
INACTIVE INGREDIENTS: STEARIC ACID 1 mg/85 g; ALLANTOIN 1 mg/85 g; COCONUT OIL 1 mg/85 g; SODIUM BICARBONATE 1 mg/85 g; OLIVE OIL 1 mg/85 g; SHEA BUTTER 1 mg/85 g; ALOE VERA LEAF 1 mg/85 g; GLYCERIN 1 mg/85 g; ISOPROPYL PALMITATE 1 mg/85 g; LECITHIN, SUNFLOWER 1 mg/85 g

BiEST 2.5 Estrogen Cream

DRUG FACTS

Active Ingredients

Micronizrd Estriol USP (Wild Yam) .2%

Micronizrd Estradiol USP (Wild Yam) .05%

PURPOSE

This is a topical cream that contains bio-identical estriol and estradiol derived from wild yam and formulated in an 80:20 ratio. When applied to the skin it can help balance your hormones and provide temporary relief from menopausal symptoms such as hot flashes.

INDICATIONS AND USAGE

This is a topical cream that contains bio-identical estriol and estradiol derived from wild yam and formulated in an 80:20 ratio. When applied to the skin it can help balance your hormones and provide temporary relief from menopausal symptoms such as hot flashes.

WARNINGS

For external cosmetic use only. If pregnant or nursing, consult a healthcare professional before using this product. Cease using this product and seek medical attention if skin irritation or other negative reactions occur. Do not use if tamper-evident seal is broken or missing. California Prop 65 Law requires this statement:

This product contains estrogen, a chemical known only to the state of California to cause cancer.

KEEP OUT OF REACH OF CHILDREN.

PREGNANCY OR BREAST FEEDING

If pregnant or nursing or if you have a serious medical condition consult a healthcare professional before using this product.

Keep Out of Reach of Children.

DOSAGE AND ADMINISTRATION

Apply once or twice a day. Massage into inner arms, thighs, chest or apply to inner forearm and rub arms together or use as directed by you physician.

INACTIVE INGREDIENT

Purified Water, Glycerin (Plant Source-Kosher), Aloe Vera
Gel,Caprylic/Capric Triglyceride,Stearic Acid, MSM
(Methylsulfonylmethane), Olive Oil, Coconut Oil, Isopropyl
Palmitate, Stearyl Alcohol, Vitamin E, Herbal-Active
(Natural Preservstive), Radish Extract (Natural
Preservative), Carbomer, Allantoin, Shea Butter, Sunflower
Lecithin, Sodium Bicarbonate.

Questions?

care@biolabspro.com

www.biolabspro.com